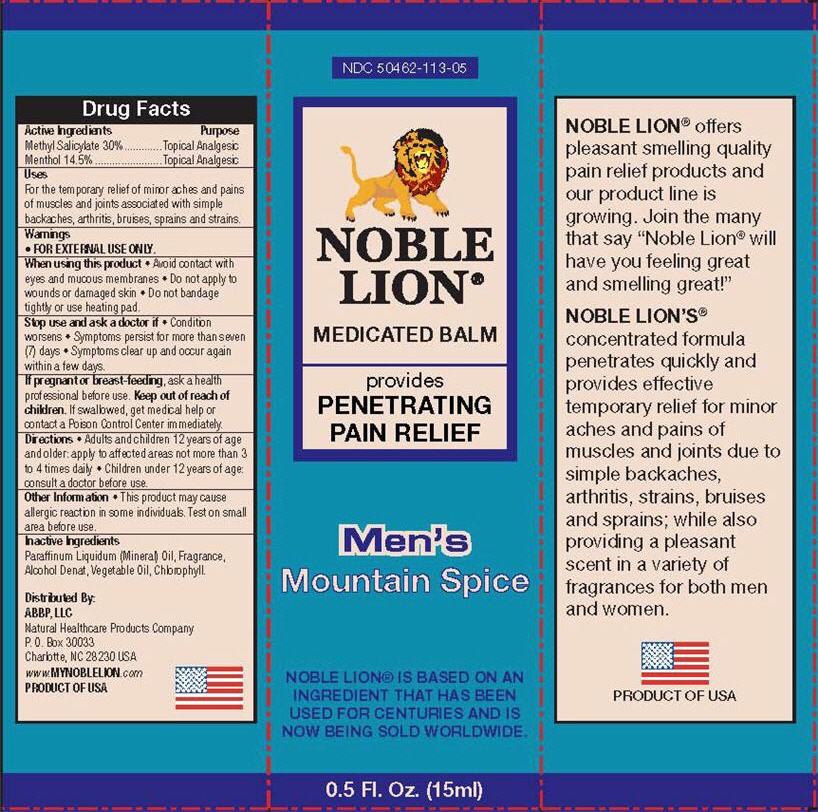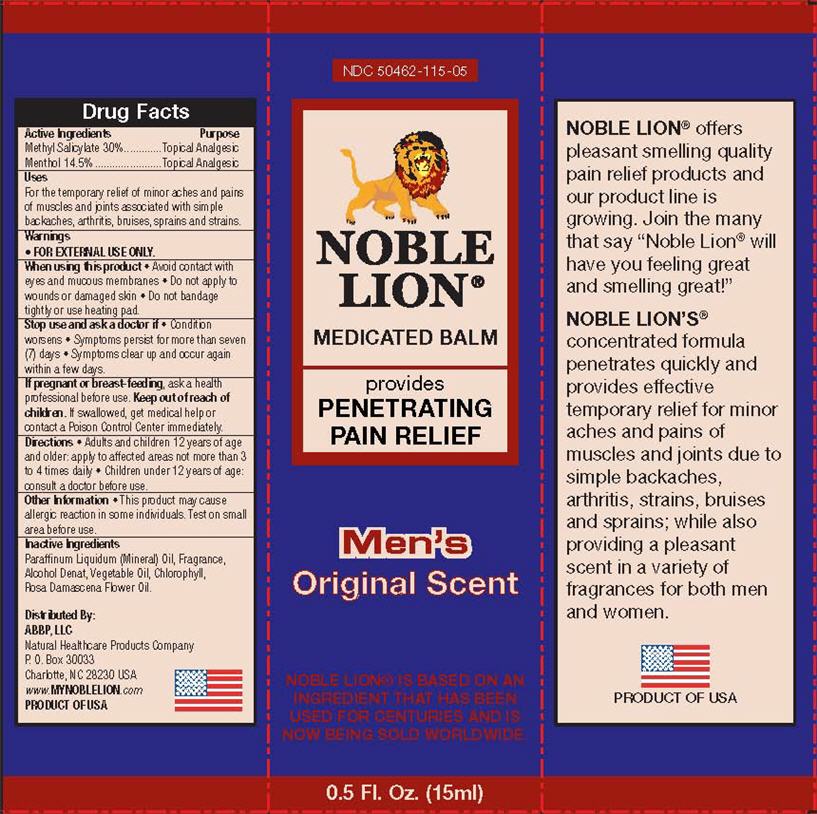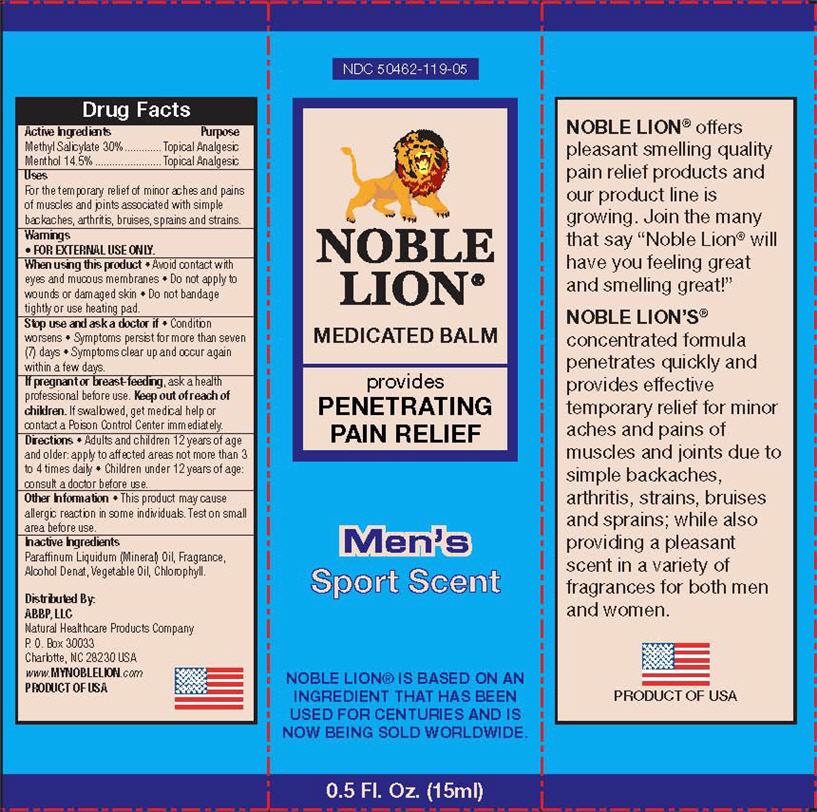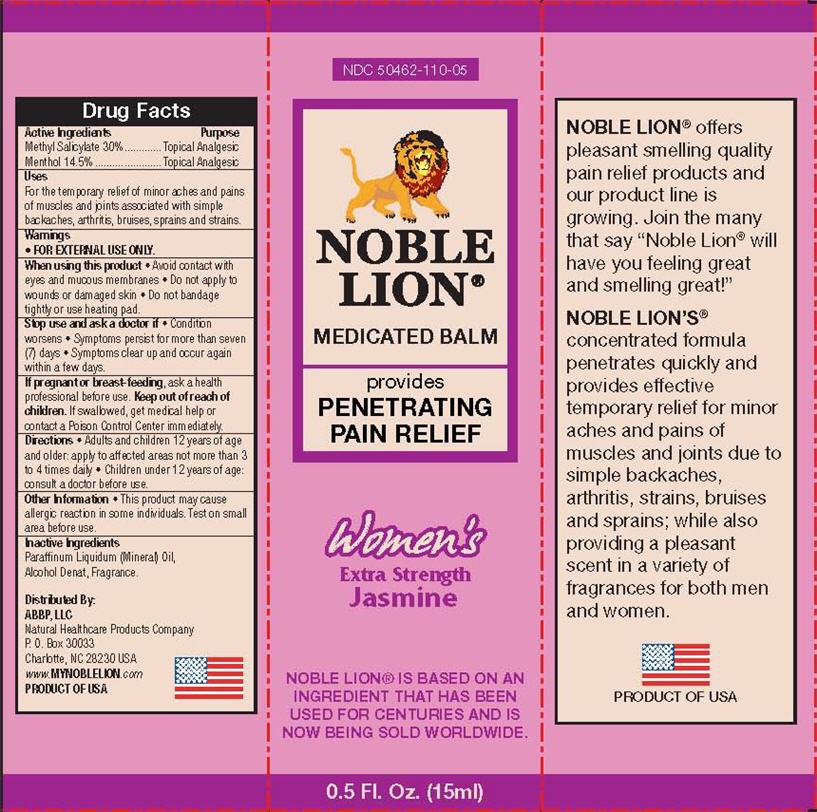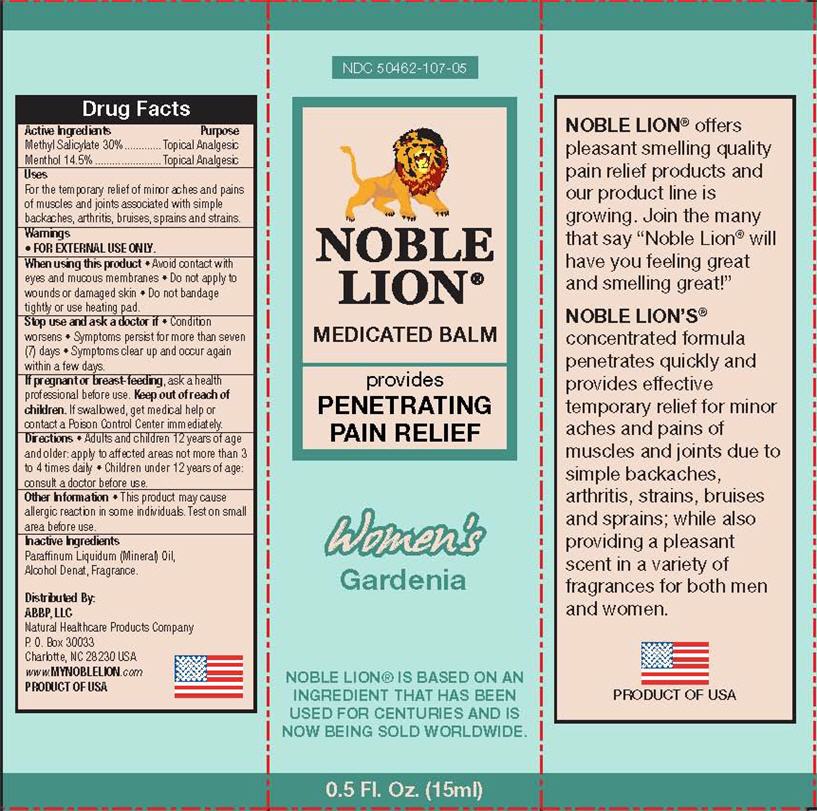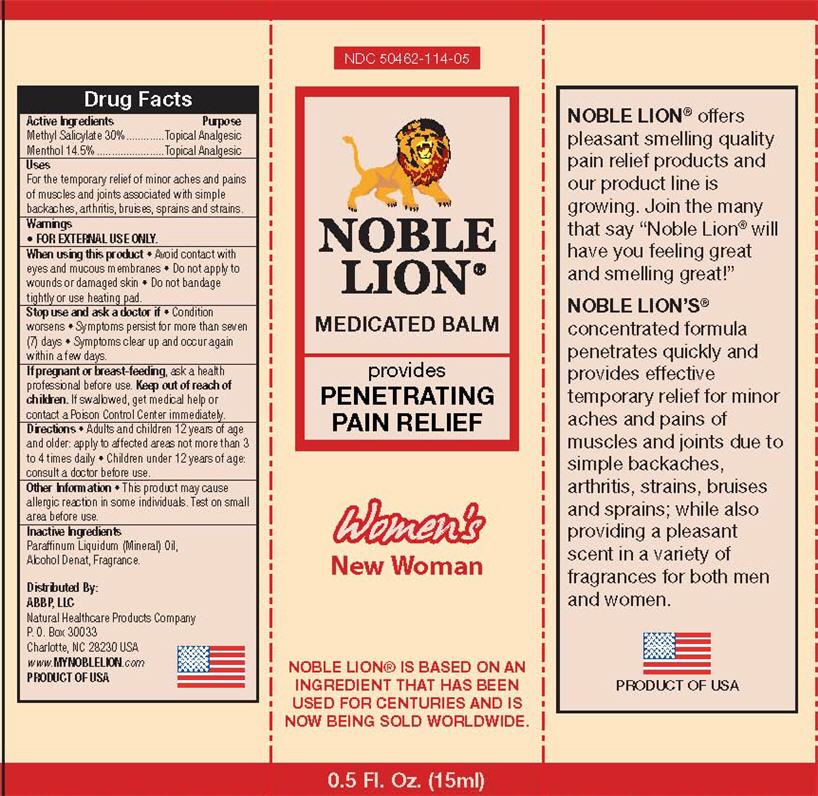 DRUG LABEL: Noble Lion Medicated Balm
NDC: 50462-113 | Form: LINIMENT
Manufacturer: ABBP (ARRINGTON, BATTLE, BELL & PERRY), LLC
Category: otc | Type: HUMAN OTC DRUG LABEL
Date: 20120621

ACTIVE INGREDIENTS: METHYL SALICYLATE 30 mL/100 mL; MENTHOL 14.5 mL/100 mL
INACTIVE INGREDIENTS: MINERAL OIL; ALCOHOL; CORN OIL

Noble Lion® Medicated Balm

Active ingredient

Methyl Salicylate 30%

Menthol 14.5%

Purpose

Topical Analgesic

Uses

For the temporary relief of minor aches and pains of muscles and joints associated with simple backaches, arthritis, bruises, sprains and strains.

Warnings

- FOR EXTERNAL USE ONLY

When using this product

- Avoid contact with eyes and mucous membranes
- Do not apply to wounds or damaged skin
- Do not bandage tightly or use heating pad.

Stop use and ask a doctor if

- Condition worsens
- Symptoms persist for more than seven (7) days
- Symptoms clear up and occur again within a few days.

If pregnant or breast-feeding,

ask a health professional before use.

Keep Out of Reach of Children

If swallowed, get medical help or contact a Poison Control Center immediately.

Directions

- Adults and children 12 years of age and older: apply to affected areas not more than 3 to 4 times daily
- Children under 12 years of age: consult a doctor before use.

Other Information

- This product may cause allergic reaction in some individuals. Test on small area before use.

Inactive ingredients

Men's Mountain Spice

Paraffinum Liquidum (Mineral) Oil, Alcohol Denat, Chlorophyll, Vegetable Oil, and Fragrance

Men's Original Scent

Paraffinum Liquidum (Mineral) Oil, Alcohol Denat, Chlorophyll, Vegetable Oil, Rosa Damascena Flower Oil, and Fragrance

Men's Sport Scent

Paraffinum Liquidum (Mineral) Oil, Alcohol Denat, Chlorophyll, Vegetable Oil, and Fragrance

Women's Extra Strength Jasmine

Paraffinum Liquidum (Mineral) Oil, Alcohol Denat, and Fragrance

Women's Gardenia

Paraffinum Liquidum (Mineral) Oil, Alcohol Denat, and Fragrance

Women's New Woman

Paraffinum Liquidum (Mineral) Oil, Alcohol Denat, and Fragrance

Package/Label Principal Display Panel - Men's Mountain Spice

NDC 50462-113-05

NOBLE LION

MEDICATED BALM

Provides PENETRATING PAIN RELIEF

Men's Mountain Spice

NOBLE LION IS BASED ON AN INGREDIENT THAT HAS BEEN USED FOR CENTURIES AND IS NOW BEING SOLD WORLDWIDE

0.5 Fl. Oz. (15ml)

Distributed By:

ABBP, LLC

Natural Healthcare Products Company

P.O. Box 30033

Charlotte, NC 28230 USA

www.MYNOBLELION.com

PRODUCT OF USA

Carton Label - Men's Mountain Spice

Package/Label Principal Display Panel - Men's Original Scent

NDC 50462-115-05

NOBLE LION

MEDICATED BALM

Provides PENETRATING PAIN RELIEF

Men's Original Scent

NOBLE LION IS BASED ON AN INGREDIENT THAT HAS BEEN USED FOR CENTURIES AND IS NOW BEING SOLD WORLDWIDE

0.5 Fl. Oz. (15ml)

Distributed By:

ABBP, LLC

Natural Healthcare Products Company

P.O. Box 30033

Charlotte, NC 28230 USA

www.MYNOBLELION.com

PRODUCT OF USA

Carton Label - Men's Original Scent

Package/Label Principal Display Panel - Men's Sport Scent

NDC 50462-119-05

NOBLE LION

MEDICATED BALM

Provides PENETRATING PAIN RELIEF

Men's Sport Scent

NOBLE LION IS BASED ON AN INGREDIENT THAT HAS BEEN USED FOR CENTURIES AND IS NOW BEING SOLD WORLDWIDE

0.5 Fl. Oz. (15ml)

Distributed By:

ABBP, LLC

Natural Healthcare Products Company

P.O. Box 30033

Charlotte, NC 28230 USA

www.MYNOBLELION.com

PRODUCT OF USA

Carton Label - Men's Sport Scent

Package/Label Principal Display Panel - Women's Extra Strength Jasmine

NDC 50462-110-05

NOBLE LION

MEDICATED BALM

Provides PENETRATING PAIN RELIEF

Women's Extra Strength Jasmine

NOBLE LION IS BASED ON AN INGREDIENT THAT HAS BEEN USED FOR CENTURIES AND IS NOW BEING SOLD WORLDWIDE

0.5 Fl. Oz. (15ml)

Distributed By:

ABBP, LLC

Natural Healthcare Products Company

P.O. Box 30033

Charlotte, NC 28230 USA

www.MYNOBLELION.com

PRODUCT OF USA

Carton Label - Women's Extra Strength Jasmine

Package/Label Principal Display Panel - Women's Gardenia

NDC 50462-107-05

NOBLE LION

MEDICATED BALM

Provides PENETRATING PAIN RELIEF

Women's Gardenia

NOBLE LION IS BASED ON AN INGREDIENT THAT HAS BEEN USED FOR CENTURIES AND IS NOW BEING SOLD WORLDWIDE

0.5 Fl. Oz. (15ml)

Distributed By:

ABBP, LLC

Natural Healthcare Products Company

P.O. Box 30033

Charlotte, NC 28230 USA

www.MYNOBLELION.com

PRODUCT OF USA

Carton Label - Women's Gardenia

Package/Label Principal Display Panel - Women's New Woman

NDC 50462-114-05

NOBLE LION

MEDICATED BALM

Provides PENETRATING PAIN RELIEF

Women's New Woman

NOBLE LION IS BASED ON AN INGREDIENT THAT HAS BEEN USED FOR CENTURIES AND IS NOW BEING SOLD WORLDWIDE

0.5 Fl. Oz. (15ml)

Distributed By:

ABBP, LLC

Natural Healthcare Products Company

P.O. Box 30033

Charlotte, NC 28230 USA

www.MYNOBLELION.com

PRODUCT OF USA

Carton Label - Women's New Woman